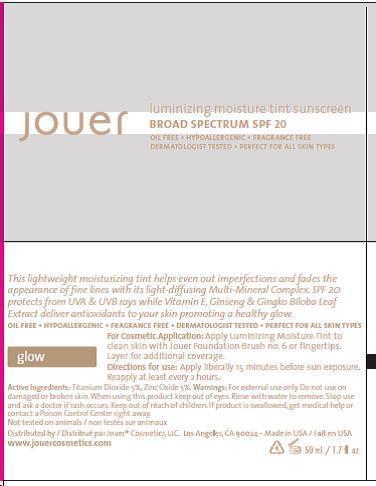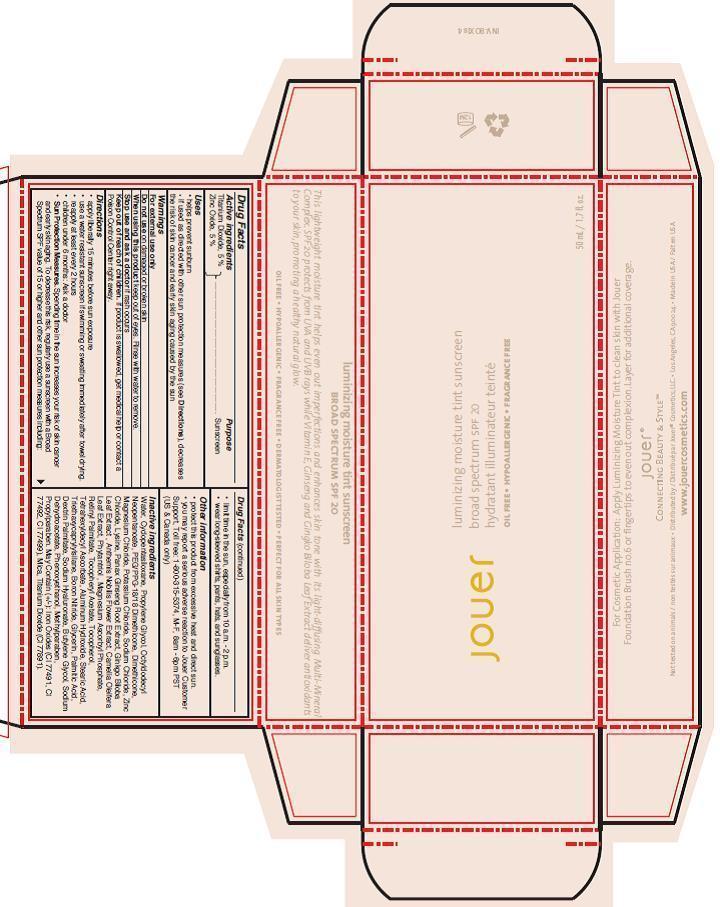 DRUG LABEL: LUMINIZING MOISTURE TINT SUNSCREEN BROAD SPECTRUM SPF 20
NDC: 69017-304 | Form: CREAM
Manufacturer: Jouer Cosmetics LLC
Category: otc | Type: HUMAN OTC DRUG LABEL
Date: 20141216

ACTIVE INGREDIENTS: TITANIUM DIOXIDE 5.0 mg/100 mL; ZINC OXIDE 5.0 mg/100 mL
INACTIVE INGREDIENTS: WATER; CYCLOMETHICONE 5; PROPYLENE GLYCOL; OCTYLDODECYL NEOPENTANOATE; PEG/PPG-18/18 DIMETHICONE; DIMETHICONE; MAGNESIUM CHLORIDE; POTASSIUM CHLORIDE; SODIUM CHLORIDE; ZINC CHLORIDE; LYSINE; ASIAN GINSENG; GINKGO; CHAMAEMELUM NOBILE FLOWER; CAMELLIA OLEIFERA LEAF; PHYTANTRIOL; MAGNESIUM ASCORBYL PHOSPHATE; VITAMIN A PALMITATE; .ALPHA.-TOCOPHEROL ACETATE; TOCOPHEROL; TETRAHEXYLDECYL ASCORBATE; ALUMINUM HYDROXIDE; STEARIC ACID; TRIETHOXYCAPRYLYLSILANE; BORON NITRIDE; GLYCERIN; PALMITIC ACID; ICODEXTRIN; SODIUM HYDROXIDE; BUTYLENE GLYCOL; SODIUM DEHYDROACETATE; PHENOXYETHANOL; METHYLPARABEN; PROPYLPARABEN; MICA; FERRIC OXIDE RED; FERRIC OXIDE YELLOW; FERROSOFERRIC OXIDE

Lumininizing moisture tint sunscreen broad spectrum SPF 20 "Glow"

ACTIVE INGREDIENT

Titanium Dioxide 5%

Zinc Oxide 5%

PURPOSE

Sunscreen

Uses

Helps prevent sunburns

If used as directed with other sun protection measures (see Directions), decreases the risk of skin cancer and early skin aging caused by the sun.

Warnings

WARNINGS

For external use only

Do not use on damages or broken skin

Stop use and ask a doctor if rash occurs

When using this product keep out of eyes. Rinse with water to remove.

Keep out of reach of children. If swallowed, get medical help or contact a poison control center right away

Directions

apply liberally 15 minutes before sun exposure

use a water resistant sunscreen if swimming or sweating: Immediately after towel drying.

reapply at least every 2 hours.

Children under 6 months. Ask a doctor

Sun Protection Measures. Spending time in the sun increases your risk of skin cancer

and early skin aging. To decrease this risk, regularly use a sunscreen with a Broad

Spectrum SPF value of 15 or higher and other sun protection measure including:

limit time in the sun, especially from 10 a.m. to 2 p.m.

wear long-sleeved shirts, pants, hats, and sunglasses

OTHER SAFETY INFORMATION

protect this product from excessive heat and direct sun.

ADVERSE REACTIONS

-you may report a serious adverse reaction to Jouer Customer support, toll free: 1-800-315-5374, M-F, 8am-6pm PST (US and Canada Only)

INACTIVE INGREDIENT

Water, Cyclopentasiloxane, Propylene Glycol, Octyldodecyl Neopentanoate, PEG/PPG 18/18 Dimethicone, Dimethicone, Magnesium Chloride, Potassium Chloride, Sodium Chloride, Zinc Chloride, Lysine, Panax Ginseng Root Extract, Ginkgo Biloba Leaf Extract, Anthemis Nobilis Flower Extract, Camellia Oleifera Leaf Extract, Phytantriol, Magnesium Ascorbyl Phosphate, Retinyl Palmitate, Tocopheryl Acetate, Tocopherol, Tetrahexyldecyl Ascorbate, Aluminum Hydroxide, Stearic Acid, Triethoxycaprylylsilane, Boron Nitride, Glycerin, Palmitic Acid, Dextrin Palmitate, Sodium Hyaluronate, Butylene Glycol, Sodium Dehydroacetate, Phenoxyethanol, Methylparaben, Propylparaben, Mica, Titanium Dioxide (CI 77891), Iron Oxide (CI 77491, CI77492, CI77499)